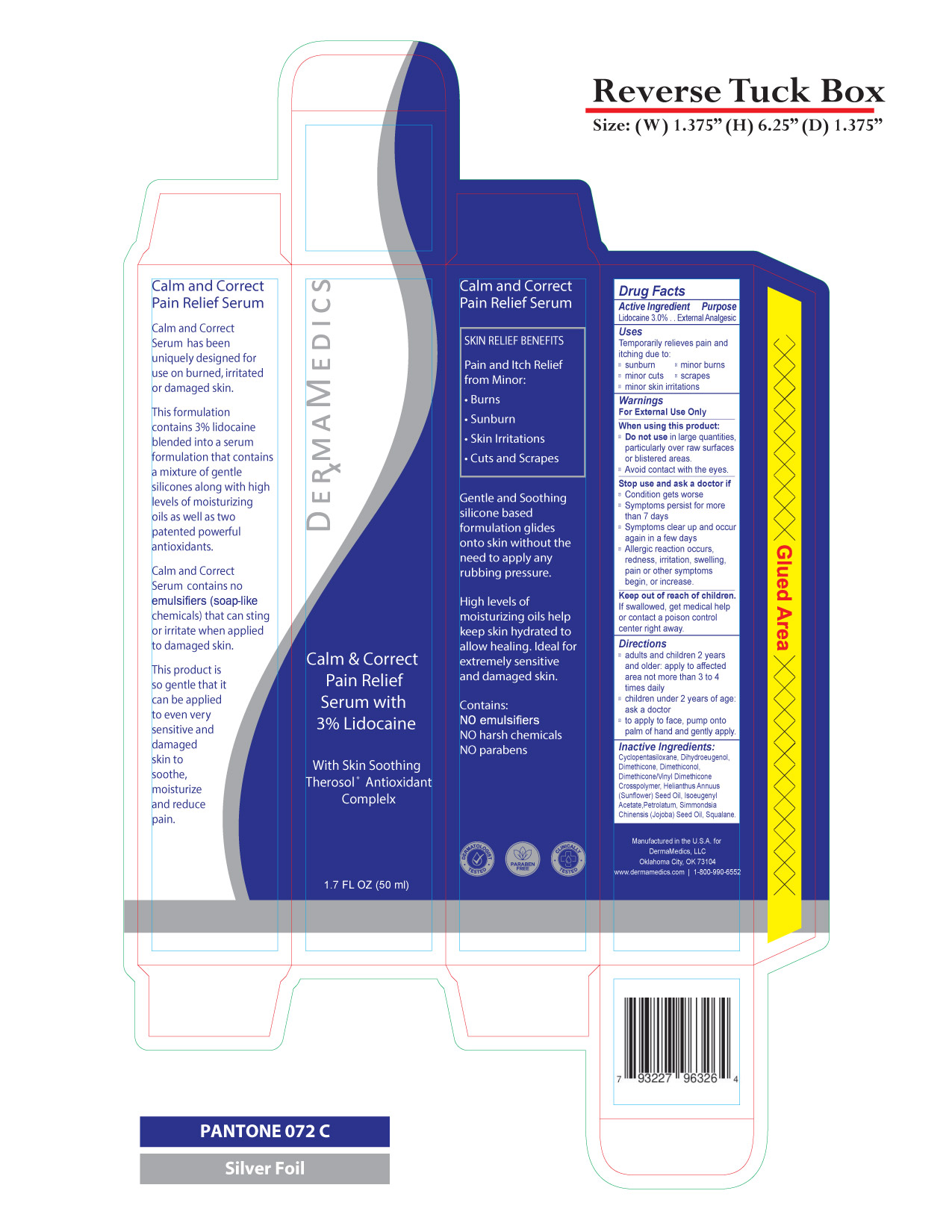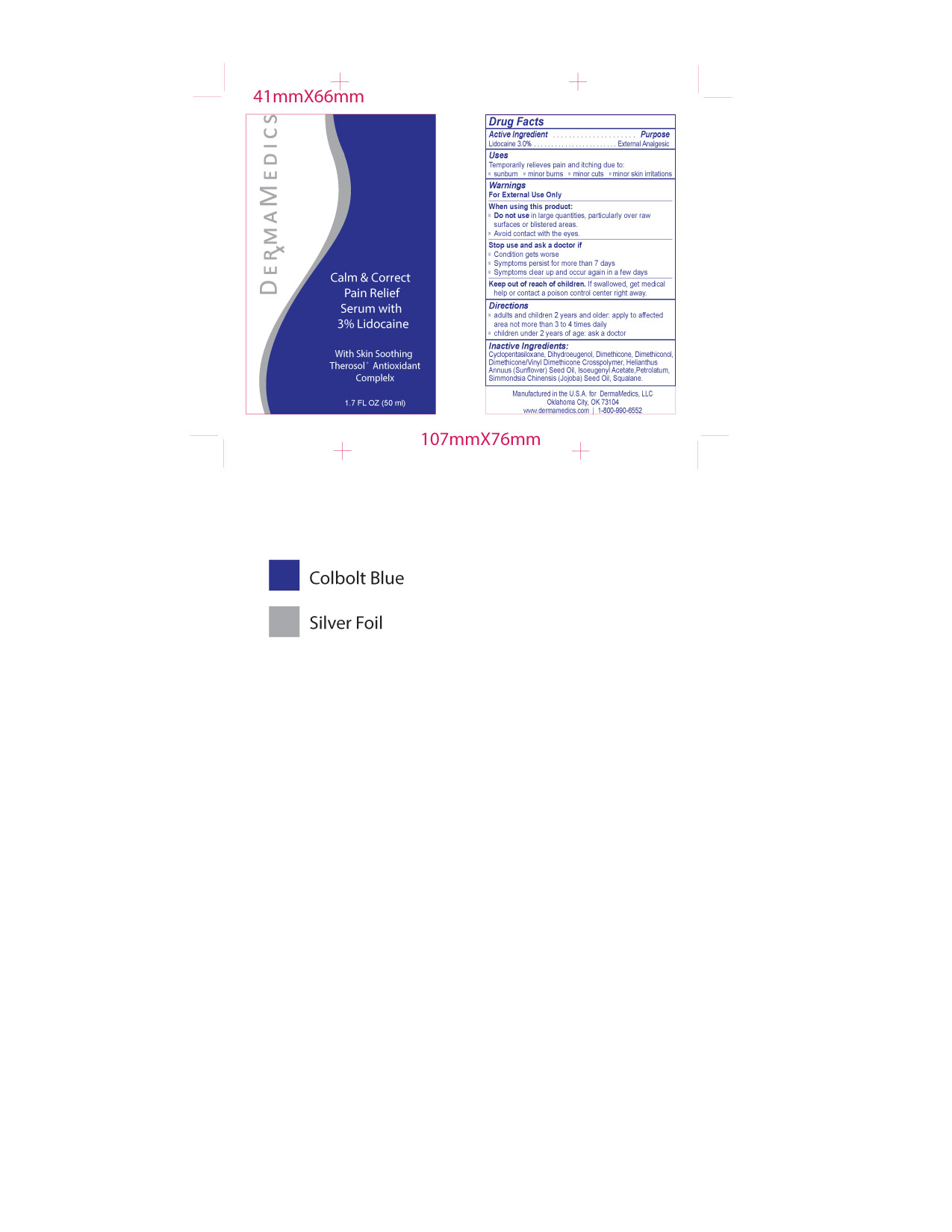 DRUG LABEL: Calm and Correct Serum with Lidocaine
NDC: 76348-725 | Form: LIQUID
Manufacturer: Renu Laboratories, LLC
Category: otc | Type: HUMAN OTC DRUG LABEL
Date: 20250509

ACTIVE INGREDIENTS: LIDOCAINE 1.5 g/50 mL
INACTIVE INGREDIENTS: CYCLOMETHICONE 5; PETROLATUM; JOJOBA OIL; DIMETHICONE; DIMETHICONE/VINYL DIMETHICONE CROSSPOLYMER (SOFT PARTICLE); ISOEUGENYL ACETATE; SQUALANE; DIHYDROEUGENOL; SUNFLOWER OIL

CALM and CORRECT PAIN RELIEF SERUM

Active Ingredient

Lidocaine 3%

Purpose

External Analgesic

Uses

Temporarily relieves pain and itching due to

- sunburn
- minor burns
- minor cuts
- minor skin irritations

Warnings

For external use only

Stop use and ask a doctor if

- Condition gets worse
- Symptoms persist for more than 7 days
- Symptoms clear up and occur again in a few days

Keep out of reach of children

If swallowed - get medical help or contact a poison control center right away

Directions

- adults and children 2 years and older apply to affected area not more than 3 to 4 times daily
- children under 2 years of age : ask a doctor

Inactive Ingredients:

Cyclopentasiloxane, Dihydroeugenol, Dimethicone, Dimethiconol, Dimethicone/Vinyl Dimethicone Crosspolymer, Helianthus Annuus (Sunflower) Seed Oil, Isoeugenyl Acetate, Petrolatum, Simmondsia Chinensis (Jojoba) Seed Oil, Squalane.

OTHER SAFETY INFORMATION

Manufactured in the U.S.A. for Dermamedics, LLC

Oklahoma City, OK 73112

www.dermamedics.com

1 800 990 6552

STATEMENT OF IDENTITY

DERMAMEDICS

Calm & Correct

Pain Relief

Serum with

3 % Lidocaine

When using this product

Do not use in large quantities particularly over raw surfaces or blistered areas

Avoid contact with the eyes

PACKAGE LABEL

BOTTLE ART AND BOX ART